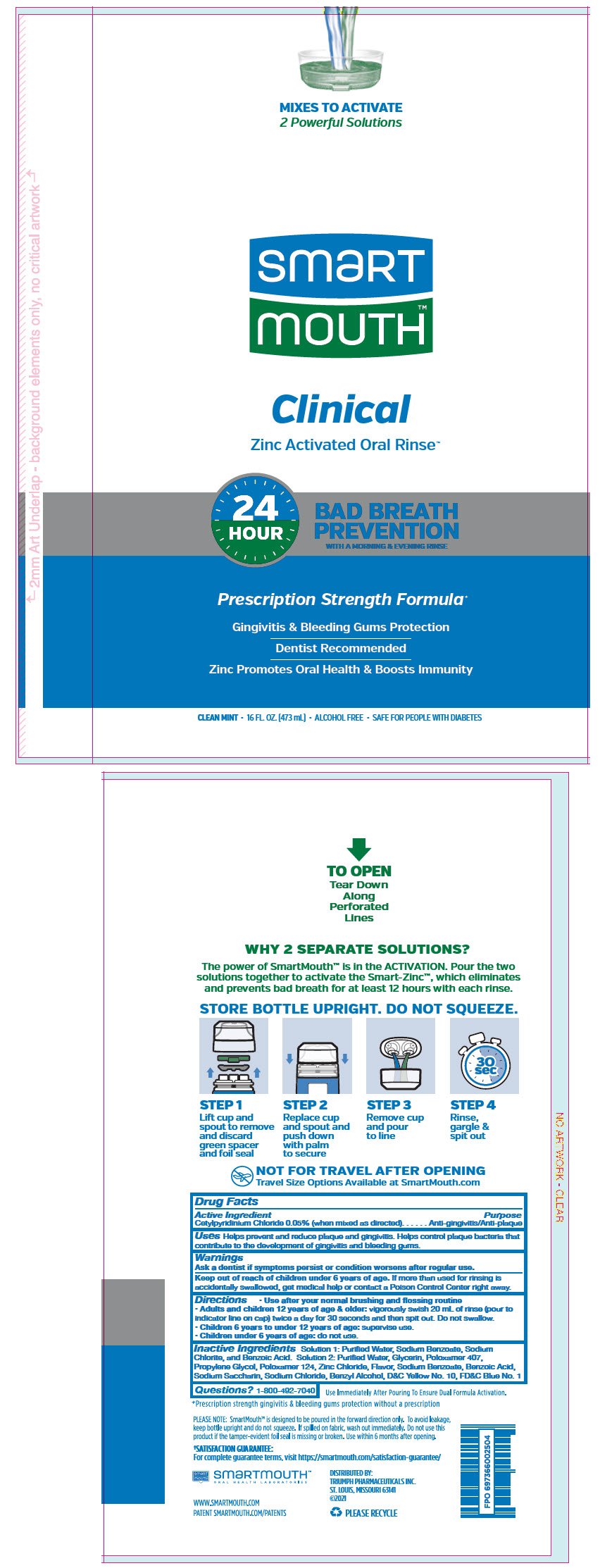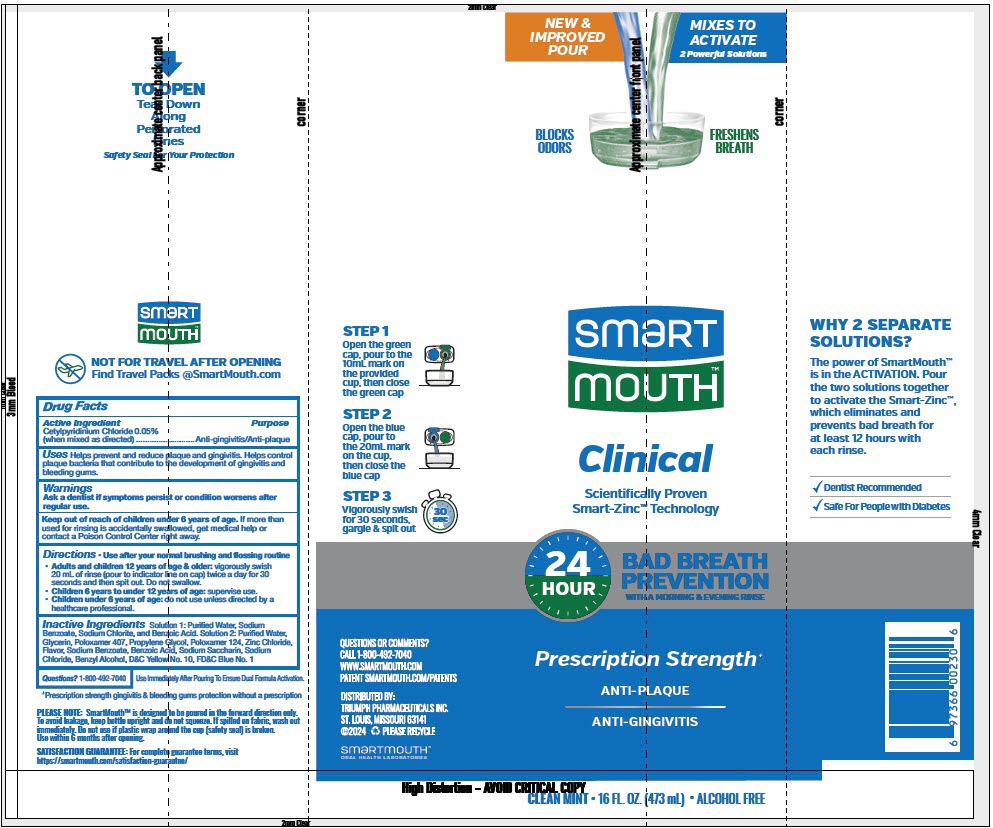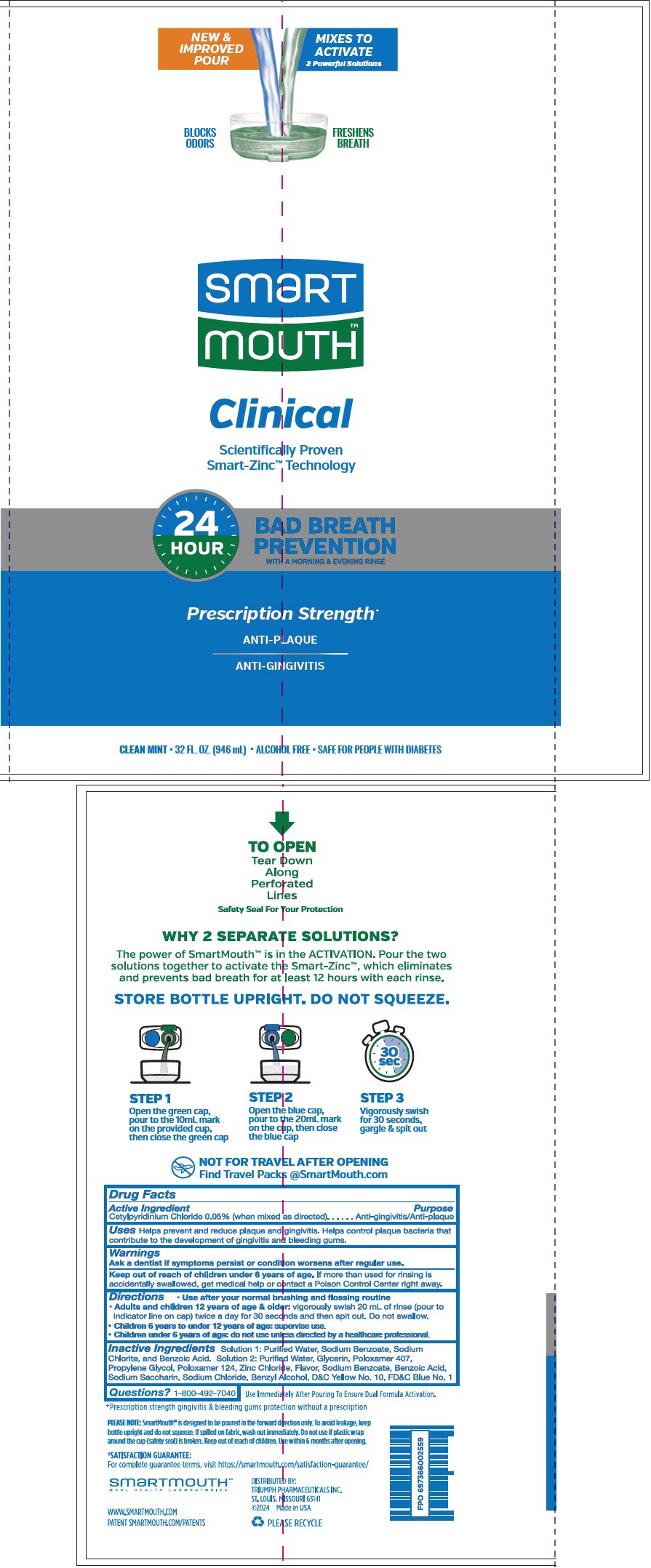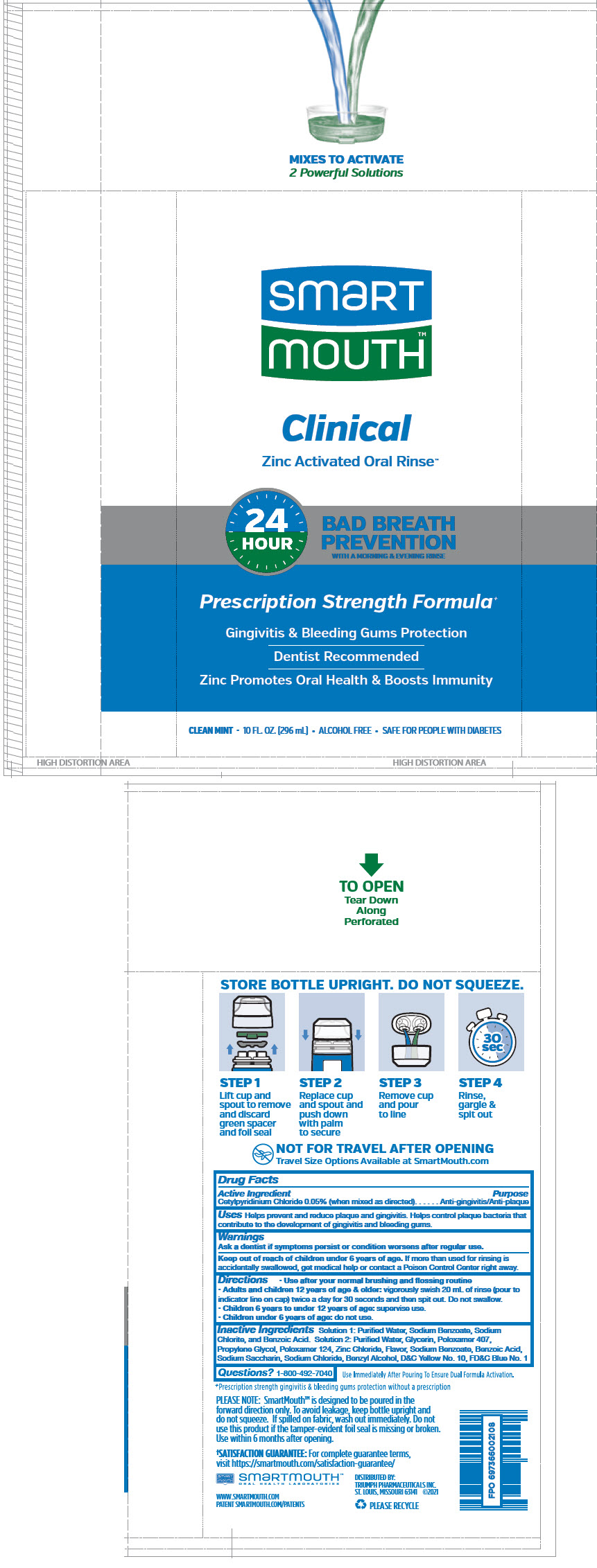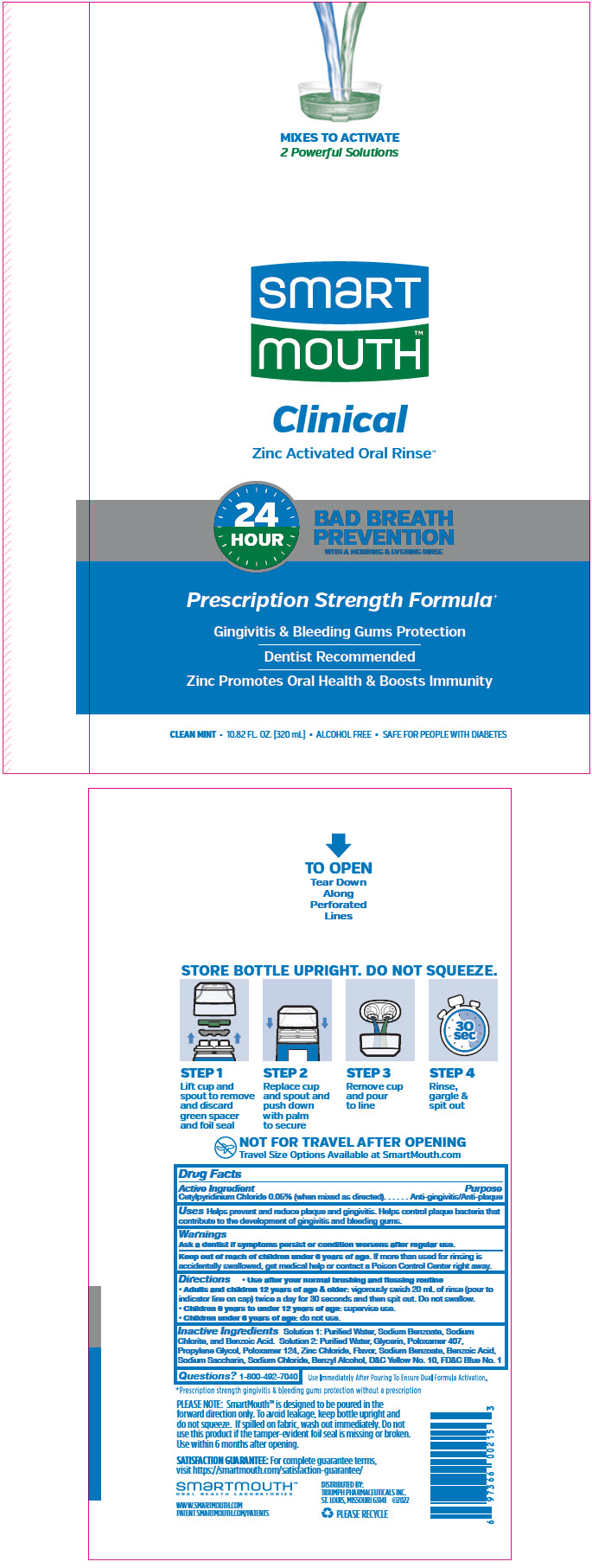 DRUG LABEL: SmartMouth 
NDC: 76357-250 | Form: KIT | Route: DENTAL
Manufacturer: Triumph Pharmaceuticals Inc.
Category: otc | Type: HUMAN OTC DRUG LABEL
Date: 20241211

ACTIVE INGREDIENTS: Cetylpyridinium Chloride 500 mg/20 mL
INACTIVE INGREDIENTS: Water; Glycerin; Poloxamer 407; Propylene Glycol; Poloxamer 124; Zinc Chloride; Sodium Benzoate; Benzoic Acid; Saccharin Sodium; Sodium Chloride; Benzyl Alcohol; D&C Yellow No. 10; FD&C Blue No. 1

SmartMouth™ Mouthwash
Gum & Plaque Formula

DRUG FACTS

Active Ingredient

Cetylpyridinium Chloride 0.05% (when mixed as directed)

Purpose

Anti-gingivitis/Anti-plaque

Uses

Helps prevent and reduce plaque and gingivitis. Helps control plaque bacteria that contribute to the development of gingivitis and bleeding gums

Warnings

ASK DOCTOR

Ask a dentist if symptoms persist or condition worsens after regular use.

Keep out of reach of children under 6 years of age.

If more than used for rinsing is accidentally swallowed, get medical help or contact a Poison Control Center right away.

Directions

- Adults and children 12 years of age and older: vigorously swish 20 milliliters of rinse (pour to indicator line on cap) twice a day for 30 seconds and then spit out. Do not swallow.
- Children 6 years to under 12 years of age: supervise use.
- Children under 6 years of age: do not use.

Other information

- This rinse is not intended to replace brushing or flossing.

Inactive Ingredients

Solution 1: Purified Water, Sodium Benzoate, Sodium Chlorite, and Benzoic Acid

Solution 2: Purified Water, Glycerin, Poloxamer 407, Propylene Glycol, Poloxamer 124, Zinc Chloride, Flavor, Sodium Benzoate, Benzoic Acid, Sodium Saccharin, Sodium Chloride, Benzyl Alcohol, D&C Yellow No. 10, FD&C Blue No. 1

Questions or comments

1-800-492-7040

DISTRIBUTED BY:
TRIUMPH PHARMACEUTICALS INC.
ST. LOUIS, MISSOURI 63114

PRINCIPAL DISPLAY PANEL - 473 mL Bottle Label - Oral Rinse

MIXES TO ACTIVATE
2 Powerful Solutions

smart
mouth™

Clinical
Zinc Activated Oral Rinse™

24
HOUR

BAD BREATH
PREVENTION
WITH A MORNING & EVENING RINSE

Prescription Strength Formula^+

Gingivitis & Bleeding Gums Protection

Dentist Recommended

Zinc Promotes Oral Health & Boosts Immunity

CLEAN MINT • 16 FL. OZ. (473 mL) • ALCOHOL FREE • SAFE FOR PEOPLE WITH DIABETES

PRINCIPAL DISPLAY PANEL - 473 mL Bottle Label - Breath Rinse

NEW &
IMPROVED
POUR

MIXES TO
ACTIVATE
2 Powerful Solutions

BLOCKS
ODORS

FRESHENS
BREATH

smart
mouth™

Clinical
Scientifically Proven
Smart-Zinc™ Technology

24
HOUR

BAD BREATH
PREVENTION
WITH A MORNING & EVENING RINSE

Prescription Strength^+

ANTI-PLAQUE

ANTI-GINGIVITIS

CLEAN MINT • 16 FL. OZ. (473 mL) • ALCOHOL FREE

PRINCIPAL DISPLAY PANEL - 946 mL Bottle Label

NEW &
IMPROVED
POUR

MIXES TO
ACTIVATE
2 Powerful Solutions

BLOCKS
ODORS

FRESHENS
BREATH

smart
mouth™

Clinical
Scientifically Proven
Smart-Zinc™ Technology

24
HOUR

BAD BREATH
PREVENTION
WITH A MORNING & EVENING RINSE

Prescription Strength^+

ANTI-PLAQUE

ANTI-GINGIVITIS

CLEAN MINT • 32 FL. OZ. (946 mL) • ALCOHOL FREE • SAFE FOR PEOPLE WITH DIABETES

PRINCIPAL DISPLAY PANEL - 296 mL Bottle Label

MIXES TO ACTIVATE
2 Powerful Solutions

smart
mouth™

Clinical
Zinc Activated Oral Rinse™

24
HOUR

BAD BREATH
PREVENTION
WITH A MORNING & EVENING RINSE

Prescription Strength Formula^+

Gingivitis & Bleeding Gums Protection

Dentist Recommended

Zinc Promotes Oral Health & Boosts Immunity

CLEAN MINT • 10 FL. OZ. (296 mL) • ALCOHOL FREE • SAFE FOR PEOPLE WITH DIABETES

PRINCIPAL DISPLAY PANEL - 320 mL Bottle Label

MIXES TO ACTIVATE
2 Powerful Solutions

smart
mouth™

Clinical
Zinc Activated Oral Rinse™

24
HOUR

BAD BREATH
PREVENTION
WITH A MORNING & EVENING RINSE

Prescription Strength Formula^+

Gingivitis & Bleeding Gums Protection

Dentist Recommended

Zinc Promotes Oral Health & Boosts Immunity

CLEAN MINT • 10.82 FL. OZ. (320 mL) • ALCOHOL FREE • SAFE FOR PEOPLE WITH DIABETES